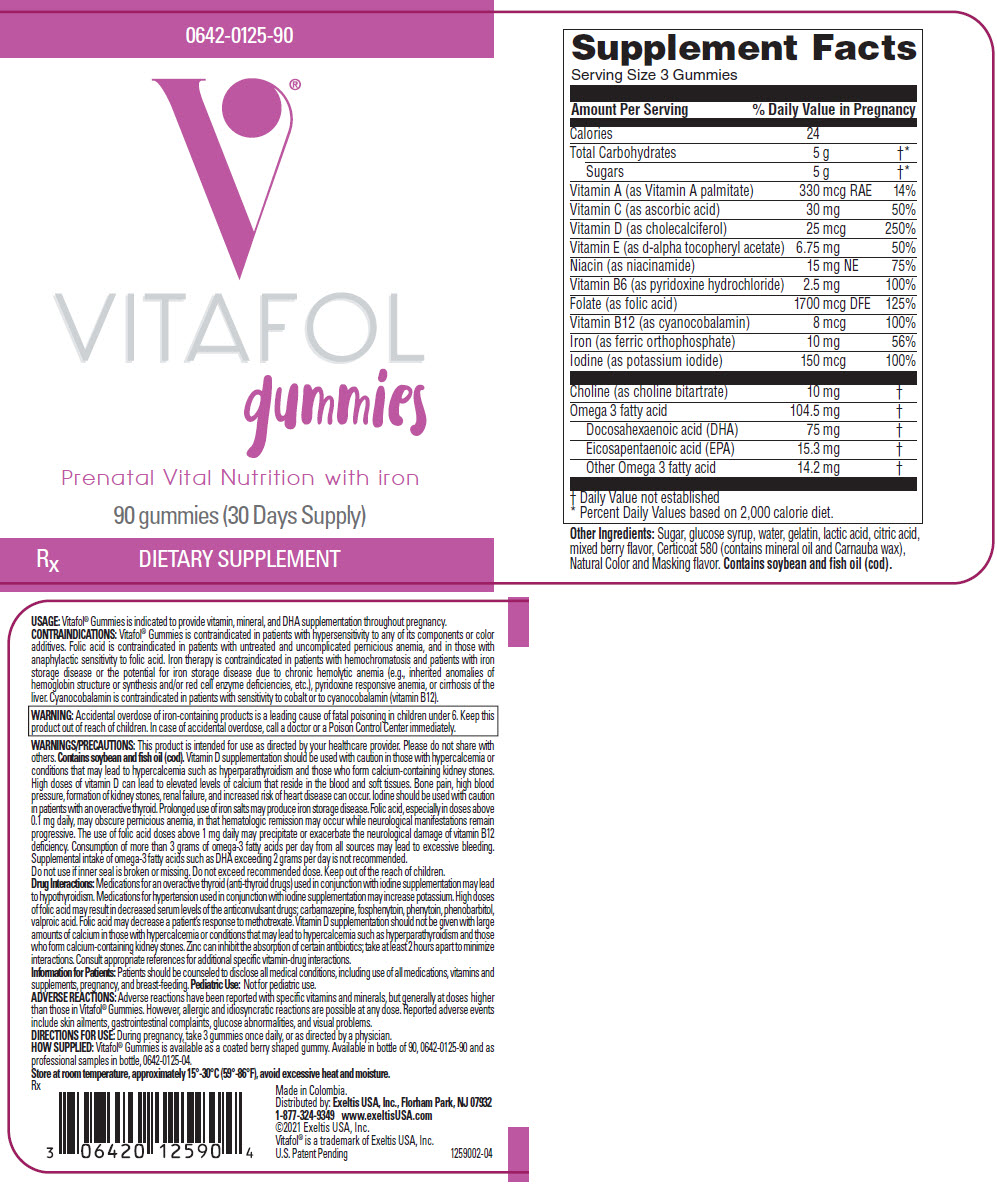 DRUG LABEL: VITAFOL Gummies
NDC: 0642-0125 | Form: TABLET, CHEWABLE
Manufacturer: Exeltis USA, Inc.
Category: other | Type: DIETARY SUPPLEMENT
Date: 20210602

ACTIVE INGREDIENTS: Vitamin A 330 ug/1 1; Ascorbic Acid 30 mg/1 1; Vitamin D 25 ug/1 1; .Alpha.-Tocopherol 6.75 mg/1 1; Niacin 15 mg/1 1; Pyridoxine Hydrochloride 2.5 mg/1 1; Folic Acid 1700 ug/1 1; Cyanocobalamin 8 ug/1 1; Iron 10 mg/1 1; Iodine 150 ug/1 1; Choline 10 mg/1 1; DOCONEXENT 75 mg/1 1; Icosapent 15.3 mg/1 1; Omega-3 Fatty Acids 14.2 mg/1 1
INACTIVE INGREDIENTS: Sucrose; Corn Syrup; Water; GELATIN, UNSPECIFIED; Lactic Acid, Unspecified Form; Citric Acid Monohydrate; Keracyanin; Propylene Glycol

Vitafol® gummies
Prenatal Supplement with Iron

HEALTH CLAIM

Rx

COMPOSITION

Amount per daily dose (3 gummies)

VITAMINS AND MINERALS:
Calories | 24
Total Carbohydrates | 5 g
Sugars | 5 g
Vitamin A (as Vitamin A palmitate) | 330 mcg RAE
Vitamin C (as ascorbic acid) | 30 mg
Vitamin D (as cholecalciferol) | 25 mcg
Vitamin E (as d-alpha tocopheryl acetate) | 6.75 mg
Niacin (as niacinamide) | 15 mg NE
Vitamin B6 (as pyridoxine hydrochloride) | 2.5 mg
Folate (as folic acid) | 1700 mcg DFE
Vitamin B12 (as cyanocobalamin) | 8 mcg
Iron (as ferric orthophosphate) | 10 mg
Iodine (as potassium iodide) | 150 mcg
Choline (as choline bitartrate) | 10 mg
Omega 3 fatty acid | 104.5 mg
Docosahexaenoic acid (DHA) | 75 mg
Eicosapentaenoic acid (EPA) | 15.3 mg
Other Omega 3 fatty acid | 14.2 mg

Other Ingredients: Sugar, glucose syrup, water, gelatin, lactic acid, citric acid, mixed berry flavor, Certicoat 580 (contains mineral oil and Carnauba wax), Natural Color and Masking flavor.

Contains soybean and fish oil (cod).

USAGE

Vitafol® Gummies is indicated to provide vitamin, mineral, and DHA supplementation throughout pregnancy.

CONTRAINDICATIONS

Vitafol® Gummies is contraindicated in patients with hypersensitivity to any of its components or color additives.

Folic acid is contraindicated in patients with untreated and uncomplicated pernicious anemia, and in those with anaphylactic sensitivity to folic acid.

Iron therapy is contraindicated in patients with hemochromatosis and patients with iron storage disease or the potential for iron storage disease due to chronic hemolytic anemia (e.g., inherited anomalies of hemoglobin structure or synthesis and/or red cell enzyme deficiencies, etc.), pyridoxine responsive anemia, or cirrhosis of the liver.

Cyanocobalamin is contraindicated in patients with sensitivity to cobalt or to cyanocobalamin (vitamin B12).

WARNINGS

WARNING: Accidental overdose of iron-containing products is a leading cause of fatal poisoning in children under 6. Keep this product out of reach of children. In case of accidental overdose, call a doctor or a Poison Control Center immediately.

WARNINGS/PRECAUTIONS

This product is intended for use as directed by your healthcare provider. Please do not share with others. Contains soybean and fish oil (cod).

Vitamin D supplementation should be used with caution in those with hypercalcemia or conditions that may lead to hypercalcemia such as hyperparathyroidism and those who form calcium-containing kidney stones. High doses of vitamin D can lead to elevated levels of calcium that reside in the blood and soft tissues. Bone pain, high blood pressure, formation of kidney stones, renal failure, and increased risk of heart disease can occur.

Iodine should be used with caution in patients with an overactive thyroid.

Prolonged use of iron salts may produce iron storage disease.

Folic acid, especially in doses above 0.1 mg daily, may obscure pernicious anemia, in that hematologic remission may occur while neurological manifestations remain progressive. The use of folic acid doses above 1 mg daily may precipitate or exacerbate the neurological damage of vitamin B12 deficiency.

Consumption of more than 3 grams of omega-3 fatty acids per day from all sources may lead to excessive bleeding.

Supplemental intake of omega-3 fatty acids such as DHA exceeding 2 grams per day is not recommended.

Do not use if inner seal is broken or missing.

Do not exceed recommended dose.

Keep out of the reach of children.

Drug Interactions

Medications for an overactive thyroid (anti-thyroid drugs) used in conjunction with iodine supplementation may lead to hypothyroidism.

Medications for hypertension used in conjunction with iodine supplementation may increase potassium.

High doses of folic acid may result in decreased serum levels of the anticonvulsant drugs; carbamazepine, fosphenytoin, phenytoin, phenobarbitol, valproic acid. Folic acid may decrease a patient's response to methotrexate.

Vitamin D supplementation should not be given with large amounts of calcium in those with hypercalcemia or conditions that may lead to hypercalcemia such as hyperparathyroidism and those who form calcium-containing kidney stones.

Zinc can inhibit the absorption of certain antibiotics; take at least 2 hours apart to minimize interactions.

Consult appropriate references for additional specific vitamin-drug interactions.

Information for Patients

Patients should be counseled to disclose all medical conditions, including use of all medications, vitamins and supplements, pregnancy, and breast-feeding.

Pediatric Use

Not for pediatric use.

ADVERSE REACTIONS

Adverse reactions have been reported with specific vitamins and minerals, but generally at doses higher than those in Vitafol® Gummies. However, allergic and idiosyncratic reactions are possible at any dose. Reported adverse events include skin ailments, gastrointestinal complaints, glucose abnormalities, and visual problems.

DIRECTIONS FOR USE

During pregnancy, take 3 gummies once daily, or as directed by a physician.

HOW SUPPLIED

Vitafol® Gummies is available as a coated berry shaped gummy. Available in bottle of 90, Item No. 0642-0125-90 and as professional samples, in bottle with 3 gummies, Item No. 0642-0125-04.

Store at room temperature, approximately 15°-30°C (59°-86°F), avoid excessive heat and moisture.

You should call your doctor for medical advice about serious adverse events. To report a serious adverse event or obtain product information, contact 1-877-324-9349

HEALTH CLAIM

Made in Colombia.
Distributed by:
Exeltis USA, Inc.
Florham Park, NJ 07932
1-877-324-9349

www.exeltisUSA.com
©2021 Exeltis USA, Inc.

These statements have not been evaluated by the Food and Drug Administration. This product is not intended to diagnose, treat, cure, or prevent any disease.

Vitafol® is a trademark of Exeltis USA, Inc.
U.S. Patent Pending

Rev. April 2021
1250301-04

PRINCIPAL DISPLAY PANEL - 90 Tablet Bottle Label

0642-0125-90

VITAFOL
gummies

Prenatal Vital Nutrition with iron

90 gummies (30 Days Supply)

RX
DIETARY SUPPLEMENT